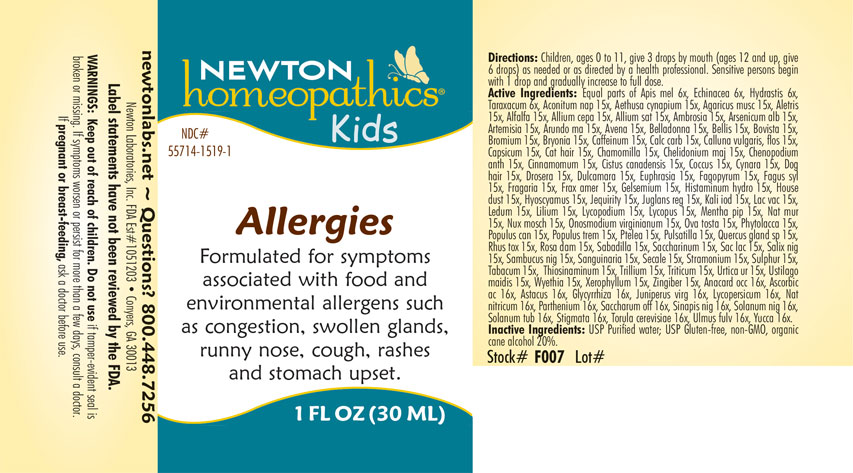 DRUG LABEL: Allergies
NDC: 55714-1519 | Form: LIQUID
Manufacturer: Newton Laboratories, Inc.
Category: homeopathic | Type: HUMAN OTC DRUG LABEL
Date: 20240307

ACTIVE INGREDIENTS: ULMUS RUBRA BARK 16 [hp_X]/1 mL; EGG SHELL, COOKED 15 [hp_X]/1 mL; SCHOENOCAULON OFFICINALE SEED 15 [hp_X]/1 mL; SAMBUCUS NIGRA FLOWERING TOP 15 [hp_X]/1 mL; SANGUINARIA CANADENSIS ROOT 15 [hp_X]/1 mL; LYCOPUS VIRGINICUS 15 [hp_X]/1 mL; LACTOSE, UNSPECIFIED FORM 15 [hp_X]/1 mL; CLAVICEPS PURPUREA SCLEROTIUM 15 [hp_X]/1 mL; TRILLIUM ERECTUM ROOT 15 [hp_X]/1 mL; ASCORBIC ACID 16 [hp_X]/1 mL; BLACK MUSTARD SEED 16 [hp_X]/1 mL; DATURA STRAMONIUM 15 [hp_X]/1 mL; TOBACCO LEAF 15 [hp_X]/1 mL; ALLYLTHIOUREA 15 [hp_X]/1 mL; URTICA URENS 15 [hp_X]/1 mL; ELYMUS REPENS ROOT 15 [hp_X]/1 mL; USTILAGO MAYDIS 15 [hp_X]/1 mL; WYETHIA HELENIOIDES ROOT 15 [hp_X]/1 mL; XEROPHYLLUM ASPHODELOIDES 15 [hp_X]/1 mL; APIS MELLIFERA 6 [hp_X]/1 mL; TARAXACUM OFFICINALE 6 [hp_X]/1 mL; ACONITUM NAPELLUS 15 [hp_X]/1 mL; AETHUSA CYNAPIUM 15 [hp_X]/1 mL; AMANITA MUSCARIA FRUITING BODY 15 [hp_X]/1 mL; ALETRIS FARINOSA ROOT 15 [hp_X]/1 mL; ALFALFA 15 [hp_X]/1 mL; ONION 15 [hp_X]/1 mL; GARLIC 15 [hp_X]/1 mL; AMBROSIA ARTEMISIIFOLIA 15 [hp_X]/1 mL; ARSENIC TRIOXIDE 15 [hp_X]/1 mL; ARTEMISIA VULGARIS ROOT 15 [hp_X]/1 mL; ARUNDO PLINIANA ROOT 15 [hp_X]/1 mL; AVENA SATIVA FLOWERING TOP 15 [hp_X]/1 mL; ATROPA BELLADONNA 15 [hp_X]/1 mL; BELLIS PERENNIS 15 [hp_X]/1 mL; LYCOPERDON UTRIFORME FRUITING BODY 15 [hp_X]/1 mL; BROMINE 15 [hp_X]/1 mL; BRYONIA ALBA ROOT 15 [hp_X]/1 mL; CAFFEINE 15 [hp_X]/1 mL; OYSTER SHELL CALCIUM CARBONATE, CRUDE 15 [hp_X]/1 mL; CALLUNA VULGARIS FLOWERING TOP 15 [hp_X]/1 mL; CAPSICUM 15 [hp_X]/1 mL; FELIS CATUS HAIR 15 [hp_X]/1 mL; MATRICARIA CHAMOMILLA 15 [hp_X]/1 mL; CHELIDONIUM MAJUS 15 [hp_X]/1 mL; DYSPHANIA AMBROSIOIDES 15 [hp_X]/1 mL; CINNAMON 15 [hp_X]/1 mL; HELIANTHEMUM CANADENSE 15 [hp_X]/1 mL; PROTORTONIA CACTI 15 [hp_X]/1 mL; CYNARA SCOLYMUS LEAF 15 [hp_X]/1 mL; CANIS LUPUS FAMILIARIS HAIR 15 [hp_X]/1 mL; DROSERA ANGLICA 15 [hp_X]/1 mL; SOLANUM DULCAMARA TOP 15 [hp_X]/1 mL; EUPHRASIA STRICTA 15 [hp_X]/1 mL; FAGOPYRUM ESCULENTUM 15 [hp_X]/1 mL; FAGUS SYLVATICA NUT 15 [hp_X]/1 mL; ALPINE STRAWBERRY 15 [hp_X]/1 mL; FRAXINUS AMERICANA BARK 15 [hp_X]/1 mL; GELSEMIUM SEMPERVIRENS ROOT 15 [hp_X]/1 mL; HISTAMINE DIHYDROCHLORIDE 15 [hp_X]/1 mL; HOUSE DUST 15 [hp_X]/1 mL; HYOSCYAMUS NIGER 15 [hp_X]/1 mL; ABRUS PRECATORIUS SEED 15 [hp_X]/1 mL; JUGLANS REGIA LEAF 15 [hp_X]/1 mL; POTASSIUM IODIDE 15 [hp_X]/1 mL; COW MILK 15 [hp_X]/1 mL; RHODODENDRON TOMENTOSUM LEAFY TWIG 15 [hp_X]/1 mL; LILIUM LANCIFOLIUM WHOLE FLOWERING 15 [hp_X]/1 mL; ONOSMODIUM VIRGINIANUM 15 [hp_X]/1 mL; PHYTOLACCA AMERICANA ROOT 15 [hp_X]/1 mL; YUCCA FILAMENTOSA 16 [hp_X]/1 mL; SACCHARIN 15 [hp_X]/1 mL; ECHINACEA, UNSPECIFIED 6 [hp_X]/1 mL; GOLDENSEAL 6 [hp_X]/1 mL; TOXICODENDRON PUBESCENS LEAF 15 [hp_X]/1 mL; SALIX NIGRA BARK 15 [hp_X]/1 mL; SULFUR 15 [hp_X]/1 mL; POPULUS BALSAMIFERA LEAF BUD 15 [hp_X]/1 mL; QUERCUS ROBUR NUT 15 [hp_X]/1 mL; MENTHA PIPERITA 15 [hp_X]/1 mL; NUTMEG 15 [hp_X]/1 mL; SOLANUM LYCOPERSICUM 16 [hp_X]/1 mL; ANACARDIUM OCCIDENTALE FRUIT 16 [hp_X]/1 mL; PTELEA TRIFOLIATA BARK 15 [hp_X]/1 mL; LYCOPODIUM CLAVATUM SPORE 15 [hp_X]/1 mL; ANEMONE PULSATILLA 15 [hp_X]/1 mL; ROSA X DAMASCENA FLOWERING TOP 15 [hp_X]/1 mL; ASTACUS ASTACUS 16 [hp_X]/1 mL; GLYCYRRHIZA GLABRA 16 [hp_X]/1 mL; JUNIPERUS VIRGINIANA TWIG 16 [hp_X]/1 mL; SUCROSE 16 [hp_X]/1 mL; SODIUM NITRATE 16 [hp_X]/1 mL; SOLANUM NIGRUM WHOLE 16 [hp_X]/1 mL; SOLANUM TUBEROSUM 16 [hp_X]/1 mL; PARTHENIUM HYSTEROPHORUS 16 [hp_X]/1 mL; GINGER 15 [hp_X]/1 mL; SODIUM CHLORIDE 15 [hp_X]/1 mL; POPULUS TREMULOIDES LEAF 15 [hp_X]/1 mL; CORN SILK 16 [hp_X]/1 mL; SACCHAROMYCES CEREVISIAE 16 [hp_X]/1 mL
INACTIVE INGREDIENTS: WATER; ALCOHOL

Allergies 1519L

INDICATIONS & USAGE SECTION

Formulated for symptoms associated with food and environmental allergens such as congestion, swollen glands, runny nose, cough, rashes and stomach upset.

DOSAGE & ADMINISTRATION SECTION

Directions: Children, ages 0 to 11, give 3 drops by mouth (ages 12 and up take 6 drops) as needed or directed by a health professional. Sensitive persons begin with 1 drop and gradually increase to full dose.

OTC - ACTIVE INGREDIENT SECTION

Equal parts of Apis mellifica 6x, Echinacea 6x, Hydrastis canadensis 6x, Taraxacum officinale 6x, Aconitum napellus 15x, Aethusa cynapium 15x, Agaricus muscarius 15x, Aletris farinosa 15x, Alfalfa 15x, Allium cepa 15x, Allium sativum 15x, Ambrosia artemisiaefolia 15x, Arsenicum album 15x, Artemisia vulgaris 15x, Arundo mauritanica 15x, Avena sativa 15x, Belladonna 15x, Bellis perrenis 15x, Bovista 15x, Bromium 15x, Bryonia 15x, Caffeinum 15x, Calcarea carbonica 15x, Calluna vulgaris, flos 15x, Capsicum annuum 15x, Cat hair 15x, Chamomilla 15x, Chelidonium majus 15x, Chenopodium anthelminticum 15x, Cinnamomum 15x, Cistus canadensis 15x, Coccus cacti 15x, Cynara scolymus 15x, Dog hair 15x, Drosera 15x, Dulcamara 15x, Euphrasia officinalis 15x, Fagopyrum esculentum 15x, Fagus sylvatica 15x, Fragaria vesca 15x, Fraxinis americana 15x, Gelsemium sempervirens 15x, Histaminum hydrochloricum 15x, House dust 15x, Hyoscyamus niger 15x, Jequirity 15x, Juglans regia 15x, Kali iodatum 15x, Lac vaccinum 15x, Ledum palustre 15x, Lilium tigrinum 15x, Lycopodium clavatum 15x, Lycopus virginicus 15x, Mentha piperita 15x, Natrum muriaticum 15x, Nux moschata 15x, Onosmodium virginianum 15x, Ova tosta 15x, Phytolacca decandra 15x, Populus candicans 15x, Populus tremuloides 15x, Ptelea trifoliata 15x, Pulsatilla 15x, Quercus glandium spiritus 15x, Rhus toxicodendron 15x, Rosa damascena 15x, Sabadilla 15x, Saccharinum 15x, Saccharum lactis 15x, Salix nigra 15x, Sambucus nigra 15x, Sanguinaria canadensis 15x, Secale cornutum 15x, Stramonium 15x, Sulphur 15x, Tabacum 15x, Thiosinaminum 15x, Trillium pendulum 15x, Triticum repens 15x, Urtica urens 15x, Ustilago maidis 15x, Wyethia helenoides 15x, Xerophyllum asphodeloides 15x, Zingiber officinale 15x, Anacardium occidentale 16x, Ascorbicum acidum 16x, Astacus fluviatilis 16x, Glycyrrhiza glabra 16x, Juniperus virginiana 16x, Lycopersicum esculentum 16x, Natrum nitricum 16x, Parthenium 16x, Saccharum officinale 16x, Sinapis nigra 16x, Solanum nigrum 16x, Solanum tuberosum 16x, Stigmata maidis 16x, Torula cerevisiae 16x, Ulmus fulva 16x, Yucca filamentosa 16x.

OTC - PURPOSE SECTION

Formulated for symptoms associated with food and environmental allergens such as congestion, swollen glands, runny nose, cough, rashes and stomach upset.

INACTIVE INGREDIENT SECTION

Inactive Ingredients: USP Purified Water; USP Gluten-free, non-GMO, organic cane alcohol 20%.

QUESTIONS SECTION

newtonlabs.net - Questions? 800.448.7256

Newton Laboratories, Inc. FDA Est # 1051203 Conyers, GA 30013

WARNINGS SECTION

WARNINGS: Keep out of reach of children. Do not use if tamper-evident seal is broken or missing. If symptoms worsen or persist for more than a few days, consult a doctor. If pregnant or breast-feeding, ask a doctor before use.

OTC - PREGNANCY OR BREAST FEEDING SECTION

If pregnant or breast-feeding, ask a doctor before use.

OTC - KEEP OUT OF REACH OF CHILDREN SECTION

Keep out of reach of children.